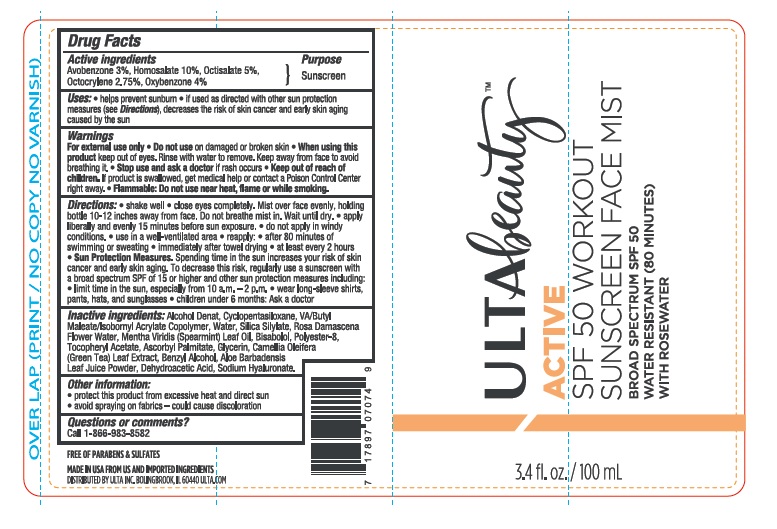 DRUG LABEL: Ulta Beauty
NDC: 58443-0254 | Form: SPRAY
Manufacturer: Prime Enterprises Inc.
Category: otc | Type: HUMAN OTC DRUG LABEL
Date: 20200117

ACTIVE INGREDIENTS: AVOBENZONE 27 mg/1 mL; HOMOSALATE 90 mg/1 mL; OCTISALATE 45 mg/1 mL; OCTOCRYLENE 24.75 mg/1 mL; OXYBENZONE 36 mg/1 mL
INACTIVE INGREDIENTS: ASCORBYL PALMITATE; ALOE VERA LEAF; CAMELLIA OLEIFERA LEAF; BENZYL ALCOHOL; DEHYDROACETIC ACID; SPEARMINT OIL; ROSA DAMASCENA FLOWER OIL; SILICA DIMETHYL SILYLATE; WATER; ISOBORNYL ACRYLATE; ALCOHOL; LEVOMENOL; CYCLOMETHICONE 5; POLYESTER-8 (1400 MW, CYANODIPHENYLPROPENOYL CAPPED); GLYCERIN; HYALURONATE SODIUM; .ALPHA.-TOCOPHEROL ACETATE

Ulta Beauty SPF 50 Workout Sunscreen Face Mist with Rosewater

Active ingredients

Avobenzone 3%

Homosalate 10%

Octisalate 5%

Octocrylene 2.75%

Oxybenzone 4%

Purpose

Sunscreen

Uses

- helps prevent sunburn
- if used as directed with other sun protection measures (see Directions), decreases the risk of skin cancer and early skin aging caused by the sun

Warnings

For external use only

- Do not use on damaged or broken skin

When using this product keep out of eyes. Rinse with water to remove. Keep away from face to avoid breathing it.

Stop use and ask a doctor if rash occurs

Keep out of reach of children. If product is swallowed, get medical help or contact a Poison Control Center right away.

Flammable: Do not use near heat, flame or while smoking.

Directions:

- shake well
- close eyes completely. Mist over face evenly, holding bottle 10-12 inches away from face. Do not breathe mist in. Wait until dry.
- apply liberally and evenly 15 minutes before sun exposure.
- do not apply in windy conditions.
- use in a well ventilated area
- reapply:
- after 80 minutes of swimming or sweating
- inmediately after towel drying
- at least every 2 hours
- Sun Protection Measures. Spending time in the sun increases your risk of skin cancer and early skin aging. To decrease this risk, regularly use a sunscreen with a broad spectrum SPF of 15 or higher and other sun protection measures including:
- limit time in the sun, especially from 10 a.m. - 2 p.m.
- wear long-sleeve shirts, pants, hats, and sunglasses
- children under 6 months: Ask a doctor

Inactive ingredients:

SD Alcohol 40-B, Cyclopentasiloxane, VA/Butyl Maleate/Isobornyl Acrylate Copolymer, Water, Silica Silylate, Rosa Damascena Flower Water, Mentha Viridis (Spearmint) Leaf Oil, Bisabolol, Polyester-8, Tocopheryl Acetate, Ascorbyl Palmitate, Glycerin, Camellia Oleifera (Green Tea) Leaf Extract, Benzyl Alcohol, Aloe Barbadensis Leaf Juice Powder, Dehydroacetic Acid, Sodium Hyaluronate.

Other Information:

- protect this product from excessive heat and direct sun
- avoid spraying on fabrics - could cause discoloration

Question or comments?

Call 1-866-983-8582